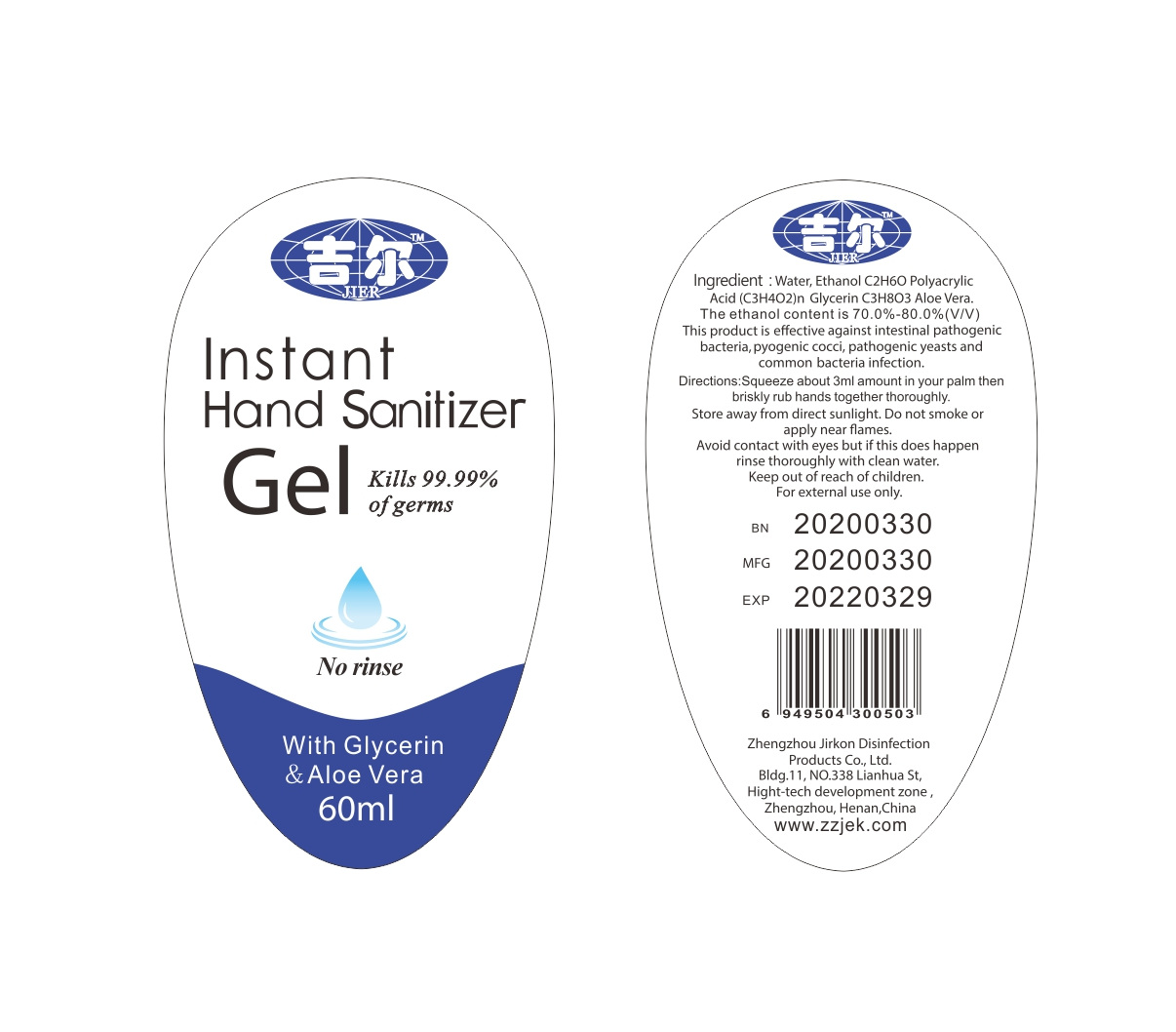 DRUG LABEL: Hand sanitizer
NDC: 54029-004 | Form: GEL
Manufacturer: ZHENGZHOU JIRKON DISINFECTION PRODUCTS CO., LTD.
Category: otc | Type: HUMAN OTC DRUG LABEL
Date: 20200513

ACTIVE INGREDIENTS: ALCOHOL 42.3 mL/60 mL
INACTIVE INGREDIENTS: WATER; GLYCERIN; CARBOMER HOMOPOLYMER, UNSPECIFIED TYPE; ALOE VERA LEAF

DOSAGE AND ADMINISTRATION

Sealed and saved in a cool and dry place.

INACTIVE INGREDIENT

Carbomer

Water

Glycerin

Aloe Vera

INDICATIONS AND USAGE

1.Surgical hand disinfection: clean hands first, then take this product 3-5ml to wet your hands, rubbing for about 3 minutes,until the liquid covering the entire surface and drying.
2.Other people hand hygiene disinfection (without water): take this product 2-3ml in the palm, rub for about 1 minute until drying.

ACTIVE INGREDIENT

Alcohol

keep out of children

PURPOSE

Disinfection
Sterilization
No Rinseing

WARNINGS

1.For external use, don't swallow , keep out of reach of children.
2.It should be far away from fire source.
3.Sealed and saved in a cool and dry place.
4.Valid for 24 months.